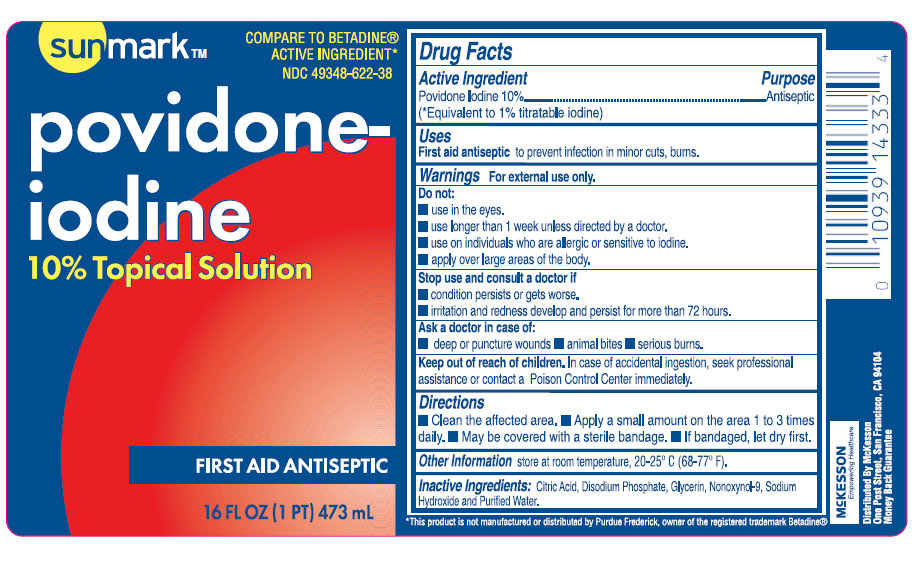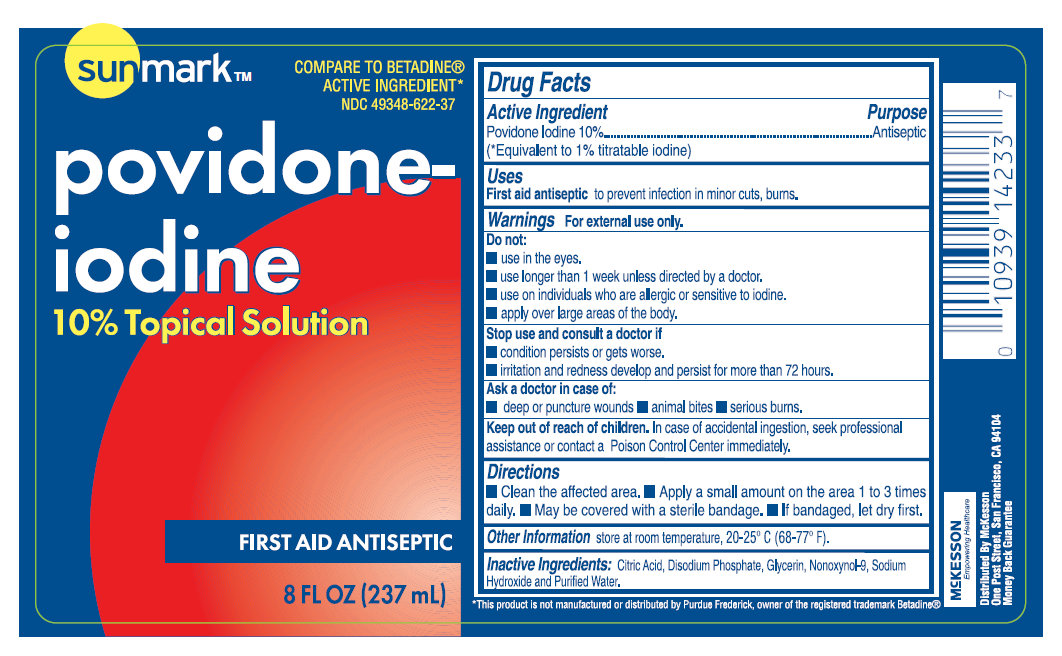 DRUG LABEL: sunmark Povidone-Iodine Topical
NDC: 49348-622 | Form: SOLUTION
Manufacturer: Strategic Sourcing Services LLC
Category: otc | Type: HUMAN OTC DRUG LABEL
Date: 20231219

ACTIVE INGREDIENTS: POVIDONE-IODINE 1 g/100 mL
INACTIVE INGREDIENTS: CITRIC ACID MONOHYDRATE; GLYCERIN; NONOXYNOL-9; SODIUM HYDROXIDE; WATER

Sunmark Povidone-Iodine 10% Topical Solution

Active Ingredient

Povidone Iodine 10% (*Equivalent to 1% titratable Iodine)

Purpose

Antiseptic

Uses

First aid antiseptic to prevent infection in minor cuts, burns.

Warnings

For external use only.

Do not:

- use in the eyes.
- use longer than 1 week unless directed by a doctor.
- use on individuals who are allergic or sensitive to iodine.
- apply over large areas of the body.

Stop use and consult a doctor if

- condition persists or gets worse.
- irritation and redness develop and persist for more than 72 hours.

Ask a doctor in case of:

- deep or puncture wounds
- animal bites
- serious burns.

Keep out of reach of children.

In case of accidental ingestion, seek professional assistance or contact a Poison Control Center immediately.

Directions

- Clean the affected area
- Apply a small amount on the area 1 to 3 times daily.
- May be covered with a sterile bandage.
- If bandaged, let dry first.

Other Information

Store at room temperature, 20-25^0 C (68-77^0 F).

Inactive Ingredients:

Citric Acid, Disodium Phosphate, Glycerin, Nonoxynol-9, Sodium Hydroxide and Purified Water.

PACKAGE LABEL

COMPARE TO BETADINE ACTIVE INGREDIENT* sunmark povidone-iodine 10% Topical Solution FIRST AID ANTISEPTIC 16 FL OZ (PT) 473mL *This product is not manufactured or distributed by Purdue Frederick, owner of the registered trademark Betadine